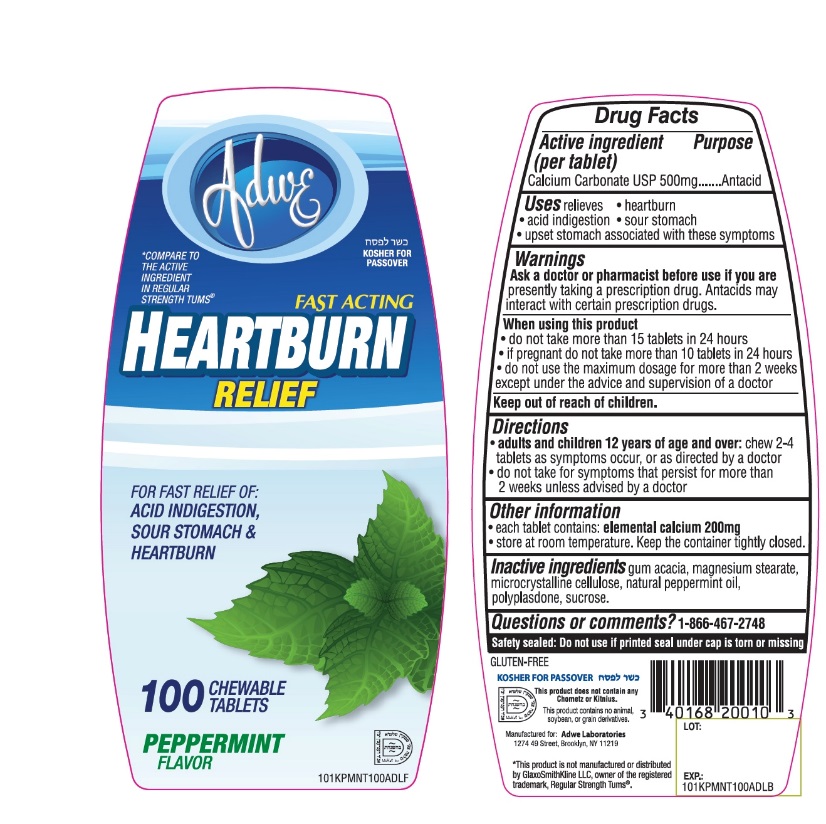 DRUG LABEL: Fast Acting Heartburn Relief

NDC: 68163-011 | Form: TABLET, CHEWABLE
Manufacturer: Raritan Pharmaceuticals Inc
Category: otc | Type: HUMAN OTC DRUG LABEL
Date: 20250717

ACTIVE INGREDIENTS: CALCIUM CARBONATE 500 mg/1 1
INACTIVE INGREDIENTS: ACACIA; MAGNESIUM STEARATE; MICROCRYSTALLINE CELLULOSE; PEPPERMINT OIL; CROSPOVIDONE (120 .MU.M); SUCROSE

ADWE Regular Strength Antacid Chewable Tablets 100 Count

Active ingredient (per tablet)

Calcium Carbonate USP 500mg

Purpose

Antacid

Uses

relieves

- heartburn
- acid indigestion
- sour stomach
- upset stomach associated with these symptoms

Warnings

Ask a doctor or pharmacist before use if you arepresently taking a prescription drug. Antacids may interact with certain prescription drugs.

When using this product

- do not take more than 15 tablets in 24 hours
- if pregnant do not take more than 10 tablets in 24 hours
- do not use the maximum dosage for more than 2 weeks except under the advice and supervision of a doctor.

Directions

- adults and children 12 years of age and older:chew 2-4 tablets as symptoms occur, or as directed by a doctor
- do not take for symptoms that persist for more than 2 weeks unless advised by a doctor

Other information

- each tablet contains: elemental calcium 200mg
- store at room temperature. Keep the container tightly closed

Inactive ingredients

Gum acacia, magnesium stearate, microcrystalline cellulose, natural peppermint oil, polyplasdone, sucrose.

Questions or comments?

1-866-467-2748

SAFETY SEALED: DO NOT USE IF PRINTED SEAL UNDER CAP IS TORN OR MISSING

Package/Label Principal Display Panel

NDC 68163-011-00

*COMPARE TO THE ACTIVE INGREDIENT IN REGULAR STRENGTH TUM®

FAST ACTING

HEARTBURN RELIEF

FOR FAST RELIEF OF:

ACID INDIGESTION, SOUR STOMACH & HEARTBURN

PEPPERMINT FLAVOR

GLUTEN FREE

100 CHEWABLE TABLETS

KOSHER FOR PASSOVER

This product does not contain any Chometz or Kitnius

This product contains no animal soybean, or grain derivatives.

Manufactured for: Adwe Laboratories

1274 49 Street, Brooklyn, NY 11219

*This product is not manufactured or distributed by GlaxoSmithKline LLC, the owner of the registered trademark Regular Strength Tums®.